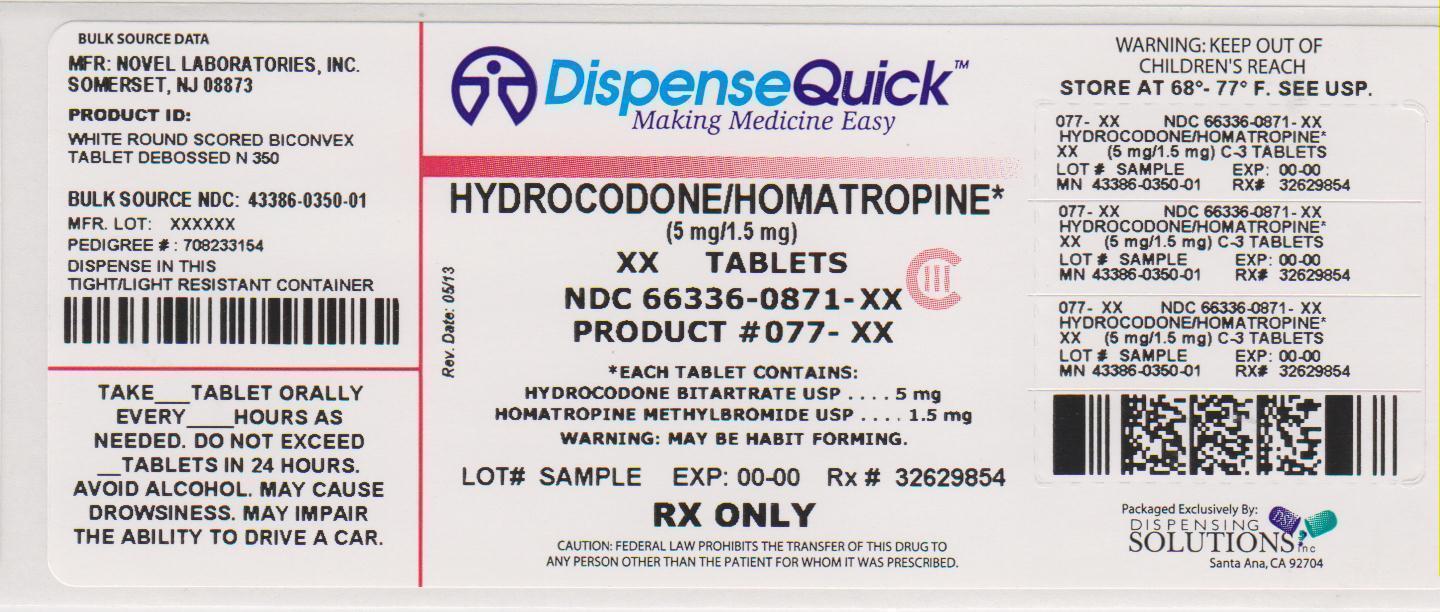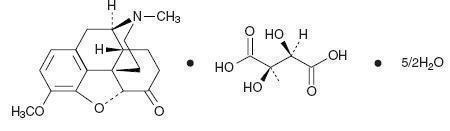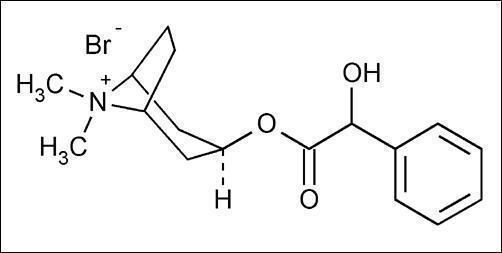 DRUG LABEL: Hydrocodone Bitartrate and Homatropine Methylbromide
NDC: 66336-871 | Form: TABLET
Manufacturer: Dispensing Solutions, Inc.
Category: prescription | Type: HUMAN PRESCRIPTION DRUG LABEL
Date: 20130625
DEA Schedule: CIII

ACTIVE INGREDIENTS: HYDROCODONE BITARTRATE 5 mg/1 1; HOMATROPINE METHYLBROMIDE 1.5 mg/1 1
INACTIVE INGREDIENTS: ANHYDROUS LACTOSE; ANHYDROUS DIBASIC CALCIUM PHOSPHATE; SODIUM STARCH GLYCOLATE TYPE A POTATO; SILICON DIOXIDE; MAGNESIUM STEARATE

Hydrocodone Bitartrate and Homatropine Methylbromide Tablets, USP

DESCRIPTION

Hydrocodone Bitartrate and Homatropine Methylbromide Tablet, USP contains hydrocodone

(dihydrocodeinone) bitartrate, a semi synthetic centrally-acting opioid antitussive. Homatropine methylbromide is included in a subtherapeutic amount to discourage deliberate overdosage.

Each Hydrocodone Bitartrate and Homatropine Methylbromide Tablet contains:

Hydrocodone Bitartrate, USP 5 mg

Homatropine Methylbromide, USP 1.5 mg

Hydrocodone Bitartrate and Homatropine Methylbromide Tablets also contain: anhydrous lactose, dicalcium phosphate anhydrous, sodium starch glycolate, colloidal silicon dioxide and magnesium stearate.

The hydrocodone component is 4,5α-epoxy-3-methoxy-17-methylmorphinan-6-one tartrate

(1:1) hydrate (2:5), a fine white crystal or crystalline powder which is derived from the opium alkaloid, thebaine, has a molecular weight of (494.50) an may be represented by the following structural formula:

C18H21NO3• C4H6O6• 2½H2O

Hydrocodone Bitartrate

Homatropine methylbromide is 8- Azoniabicyclo[3.2.1]octane, 3-[(hydroxyphenyl-acetyl)oxy]-

8, 8-dimethyl-, bromide, endo-; a white crystal or fine white crystalline powder, with a molecular weight of (370.29).

C17H24BrNO3

Homatropine Methylbromide

CLINICAL PHARMACOLOGY

Hydrocodone is a semisynthetic opioid antitussive and analgesic with multiple actions qualitatively similar to those of codeine. The precise mechanism of action of hydrocodone and other opiates is not known; however, hydrocodone is believed to act directly on the cough center. In excessive doses, hydrocodone, like other opium derivatives, will depress respiration. The effects of hydrocodone in therapeutic doses on the cardiovascular system are insignificant. Hydrocodone can produce miosis, euphoria, physical and psychological dependence.

Following a 10 mg oral dose of hydrocodone administered to five adult male subjects, the mean peak concentration was 23.6 ± 5.2 ng/ml. Maximum serum levels were achieved at 1.3 ± 0.3 hours and the half-life was determined to be 3.8 ± 0.3 hours. Hydrocodone exhibits a complex pattern of metabolism including 0-demethylation, N-demethylation and 6-keto reduction to the corresponding 6-α and 6-β-hydroxymetabolites.

INDICATIONS AND USAGE

Hydrocodone Bitartrate and Homatropine Methylbromide Tablets, USP are indicated for the symptomatic relief of cough in adults and children 6 years of age and older.

CONTRAINDICATIONS

Hydrocodone bitartrate and homatropine methylbromide tablets should not be administered to patients who are hypersensitive to hydrocodone or homatropine methylbromide.

WARNINGS

Hydrocodone can produce drug dependence of the morphine type and, therefore, has the potential for being abused. Psychic dependence, physical dependence and tolerance may develop upon repeated administration of hydrocodone bitartrate and homatropine methylbromide tablets and it should be prescribed and administered with the same degree of caution appropriate to the use of other opioid drugs (SEE DRUG ABUSE AND DEPENDENCE).

Respiratory Depression:

The use of hydrocodone bitartrate and homatropine methylbromide tablets is not recommended for use in children less than 6 years of age because of the risk of fatal respiratory depression (see ADVERSE REACTIONS – Respiratory Depression). Hydrocodone bitartrate and homatropine methylbromide tablets produce dose-related respiratory depression by directly acting on brain stem respiratory centers. If respiratory depression occurs, it may be antagonized by the use of naloxone hydrochloride and other supportive measures when indicated.

Head Injury and Increased Intracranial Pressure:

The respiratory depression properties of opioids and their capacity to elevate cerebrospinal fluid pressure may be markedly exaggerated in the presence of head injury, other intracranial lesions or a pre-existing increase in intracranial pressure. Furthermore, opioids produce adverse reactions which may obscure the clinical course of patients with head injuries.

Acute Abdominal Conditions:

The administration of hydrocodone bitartrate and homatropine methylbromide tablets or other opioids may obscure the diagnosis or clinical course of patients with acute abdominal conditions.

Pediatric Use:

In pediatric patients, as well as adults, the respiratory center is sensitive to the depressant action of opioid cough suppressants in a dose-dependent manner. Caution should be exercised when administering hydrocodone bitartrate and homatropine methylbromide tablets to pediatric patients 6 years of age and older because of the potential for fatal respiratory depression. Overdose or concomitant administration of hydrocodone bitartrate and homatropine methylbromide tablets with other respiratory depressants may increase the risk of respiratory depression in pediatric patients. Benefit to risk ratio should be carefully considered especially in the pediatric population with respiratory embarrassment (e.g., croup) (see PRECAUTIONS).

PRECAUTIONS

General:

Before prescribing medication to suppress or modify cough, it is important to ascertain that the underlying cause of cough is identified, that modification of cough does not increase the risk of clinical or physiological complications, and that appropriate therapy for the primary disease is provided.

Special Risk Patients:

Hydrocodone bitartrate and homatropine methylbromide tablets should be given with caution to certain patients such as the elderly or debilitated, and those with severe impairment of hepatic or renal functions, hypothyroidism, Addison’s disease, prostatic hypertrophy or urethral stricture, asthma, and narrow-angle glaucoma.

Information for Patients

Hydrocodone may produce marked drowsiness and impair the mental and/or physical abilities required for the performance of potentially hazardous tasks such as driving a car or operating machinery. The patient using hydrocodone bitartrate and homatropine methylbromide tablets should be cautioned accordingly. Keep out of the reach of children.

Drug Interactions

Patients receiving opioids, antihistamines, antipsychotics, antianxiety agents or other CNS depressants (including alcohol) concomitantly with hydrocodone bitartrate and homatropine methylbromide tablets may exhibit an additive CNS depression. When combined therapy is contemplated, the dose of one or both agents should be reduced.

The use of MAO inhibitors or tricyclic antidepressants with hydrocodone preparations may increase the effect of either the antidepressant or hydrocodone.

Carcinogenesis, Mutagenesis, Impairment of Fertility

Studies of hydrocodone bitartrate and homatropine methylbromide tablets in animals to evaluate the carcinogenic and mutagenic potential and the effect on fertility have not been conducted.

Pregnancy

Teratogenic Effects

Pregnancy Category C: Animal reproduction studies have not been conducted with hydrocodone bitartrate and homatropine methylbromide tablets. It is also not known whether hydrocodone bitartrate and homatropine methylbromide tablets can cause fetal harm when administered to a pregnant woman or can affect reproduction capacity. Hydrocodone bitartrate and homatropine methylbromide tablets should be given to a pregnant woman only if clearly needed.

Nonteratogenic Effects

Babies born to mothers who have been taking opioids regularly prior to delivery will be physically dependent. The withdrawal signs include irritability and excessive crying, tremors, hyperactive reflexes, increased respiratory rate, increased stools, sneezing, yawning, vomiting and fever. The intensity of the syndrome does not always correlate with the duration of maternal opioid use or dose.

Labor and Delivery

As with all opioids, administration of hydrocodone bitartrate and homatropine methylbromide tablets to the mother shortly before delivery may result in some degree of respiratory depression in the newborn, especially if higher doses are used.

Nursing Mothers

It is not known whether this drug is excreted in human milk. Because many drugs are excreted in human milk and because of the potential for serious adverse reactions in nursing infants from hydrocodone bitartrate and homatropine methylbromide tablets, a decision should be made whether to discontinue nursing or to discontinue the drug, taking into account the importance of the drug to the mother.

Pediatric Use

Safety and effectiveness of hydrocodone bitartrate and homatropine methylbromide tablets in pediatric patients under six have not been established. The use of hydrocodone bitartrate and homatropine methylbromide tablets in children less than 6 years of age has been associated with cases of fatal respiratory depression (see ADVERSE REACTIONS – Respiratory Depression). Hydrocodone bitartrate and homatropine methylbromide tablets should be used with caution in pediatric patients 6 years of age and older (see WARNINGS – Pediatric Use).

ADVERSE REACTIONS

Central Nervous System:

Sedation, drowsiness, mental clouding, lethargy, impairment of mental and physical performance, anxiety, fear, dysphoria, dizziness, psychic dependence, mood changes.

Gastrointestinal System:

Nausea and vomiting may occur; they are more frequent in ambulatory than in recumbent patients. Prolonged administration of hydrocodone bitartrate and homatropine methylbromide tablets may produce constipation.

Genitourinary System:

Ureteral spasm, spasm of vesicle sphincters and urinary retention have been reported with opiates.

Respiratory Depression:

Hydrocodone bitartrate and homatropine methylbromide tablets may produce doserelated respiratory depression by acting directly on brain stem respiratory centers (see OVERDOSAGE). Use of hydrocodone bitartrate and homatropine methylbromide tablets in children less than 6 years of age has been associated with fatal respiratory depression.

Overdose with hyodrocodone bitartrate and homatropine methylbromide tablets in children 6 years of age and older, in adolescents, and in adults has been associated with fatal respiratory depression.

Postmarketing events seen in children under 6 years of age include accidental overdose, bronchopneumonia, coma, cyanosis, death, death neonatal, dyspnea, pulmonary edema, respiratory arrest, and respiratory depression.

Postmarketing events seen in patients older than 6 years of age include accidental overdose, cardio-respiratory arrest, death due to drug toxicity, non-accidental overdose, and overdose.

Dermatological:

Skin rash, pruritus.

DRUG ABUSE AND DEPENDENCE

Hydrocodone bitartrate and homatropine methylbromide tablets are a Schedule III opioid.

Psychic dependence, physical dependence and tolerance may develop upon repeated administration of opioids; therefore, hydrocodone bitartrate and homatropine methylbromide tablets should be prescribed and administered with caution. However, psychic dependence is unlikely to develop when hydrocodone bitartrate and homatropine methylbromide tablets is used for a short time for the treatment of cough. Physical dependence, the condition in which continued administration of the drug is required to prevent the appearance of a withdrawal syndrome, assumes clinically significant proportions only after several weeks of continued oral opioid use, although some mild degree of physical dependence may develop after a few days of opioid therapy.

OVERDOSAGE

Signs and Symptoms:

Serious overdosage with hydrocodone is characterized by respiratory depression (a decrease in respiratory rate and/or tidal volume, Cheyne-Stokes respiration, cyanosis), extreme somnolence progressing to stupor or coma, skeletal muscle flaccidity, cold and clammy skin, and sometimes bradycardia and hypotension. In severe overdosage, apnea, circulatory collapse, cardiac arrest and death may occur. The ingestion of very large amounts of hydrocodone bitartrate and homatropine methylbromide tablets may, in addition, result in acute homatropine intoxication.

Treatment:

Primary attention should be given to the reestablishment of adequate respiratory exchange through provision of a patent airway and the institution of assisted or controlled ventilation. The opioid antagonist naloxone hydrochloride is a specific antidote for respiratory depression which may result from overdosage or unusual sensitivity to opioids including hydrocodone. Therefore, an appropriate dose of naloxone hydrochloride should be administered, preferably by the intravenous route, simultaneously with efforts at respiratory resuscitation. For further information, see full prescribing information for naloxone hydrochloride. An antagonist should not be administered in the absence of clinically significant respiratory depression. Oxygen, intravenous fluids, vasopressors and other supportive measures should be employed as indicated. Gastric emptying may be useful in removing unabsorbed drug.

DOSAGE AND ADMINISTRATION

Adults and Adolescents 12 years of Age and Older

One (1) tablet every 4 to 6 hours as needed; do not exceed six (6) tablets in 24 hours.

Children 6 to 11 Years of Age

One-half (1/2) tablet every 4 to 6 hours as needed; do not exceed three (3) tablets in 24 hours.

HOW SUPPLIED

Hydrocodone Bitartrate and Homatropine Methylbromide Tablets are available as white, round, scored, biconvex tablet debossed with “N” on upper side of the score, “350” on the lower side of the score and plain on the other side containing 5 mg hydrocodone bitartrate and 1.5 mg homatropine methylbromide and is available in:

Bottles of 30 NDC 43386-350-03

Bottles of 100 NDC 43386-350-01

Bottles of 500 NDC 43386-350-05

Storage and Handling

Store tablets at 20°-25°C (68°-77°F). [See USP Controlled Room Temperature.] Dispense in a tight, light-resistant container, as defined in the USP, with a child-resistant closure (as required).

Oral prescription where permitted by state law.

Manufactured by:

Novel Laboratories, Inc.

400 Campus drive

Somerset, NJ 08873

Distributed by:

GAVIS Pharmaceuticals, LLC

400 Campus drive

Somerset, NJ 08873